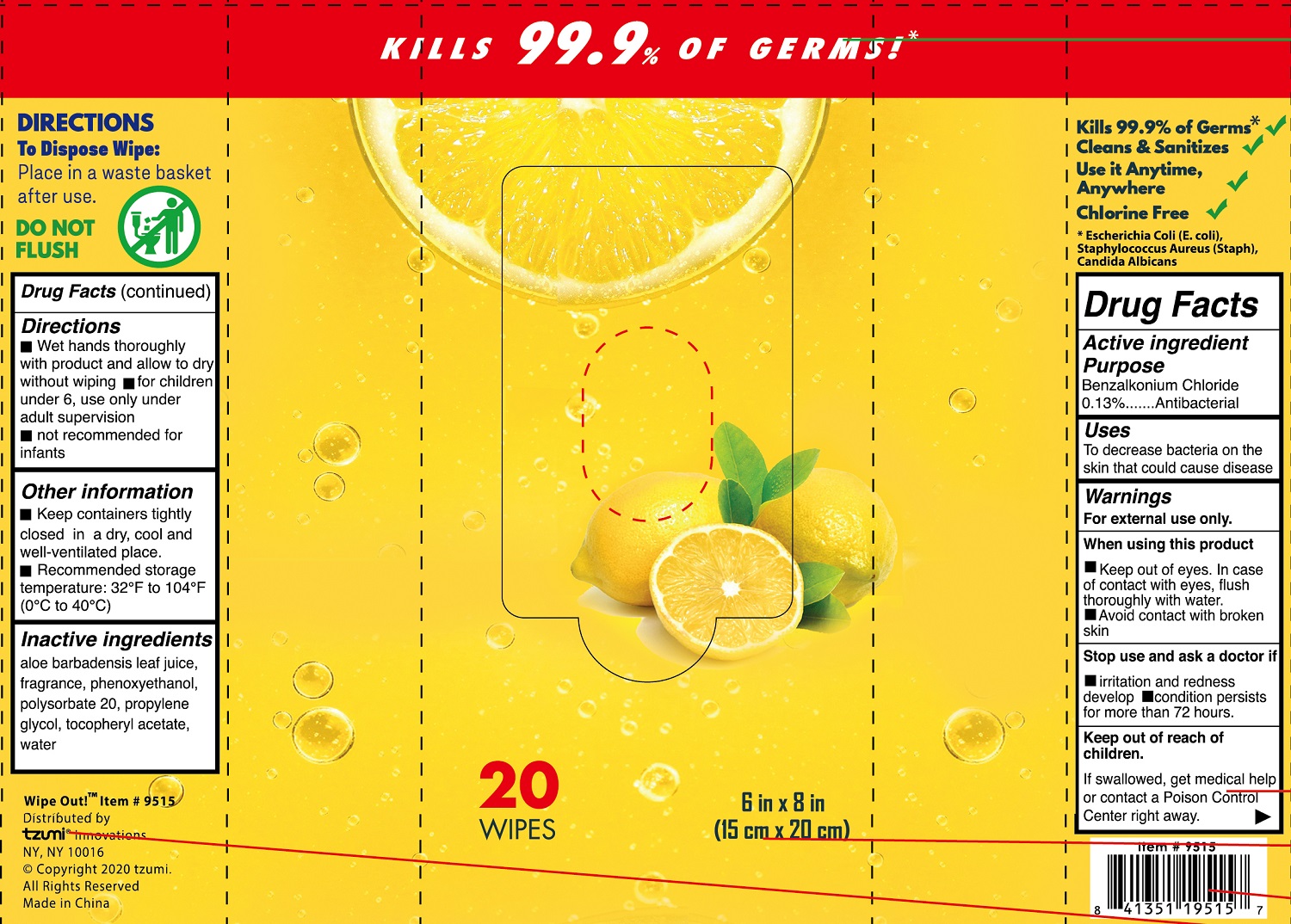 DRUG LABEL: WIPE OUT Antibacterial Wipes
NDC: 76896-002 | Form: CLOTH
Manufacturer: ZHEJIANG BINGER NONWOVEN CO., LTD.
Category: otc | Type: HUMAN OTC DRUG LABEL
Date: 20220115

ACTIVE INGREDIENTS: BENZALKONIUM CHLORIDE 0.13 g/100 g
INACTIVE INGREDIENTS: ALOE VERA LEAF; ALPHA-TOCOPHEROL ACETATE; PROPYLENE GLYCOL; FRAGRANCE LAVENDER & CHIA F-153480; PHENOXYETHANOL; POLYSORBATE 20; WATER

76896-002 WIPE OUT Antibacterial Wipes （Lemon Scent）

Active Ingredient

Benzalkonium Chloride 0.13%

Purpose

Antiacterial

USE

To decrease bacteria on the
skin that could cause disease

Warning

For external use only.
When using this product
■Keep out of eyes. In case
of contact with eyes, flush
thoroughly with water.
■Avoid contact with broken
skin
Stop use and ask a doctor if
■iritation and redness
develop■lcondition persists
for more than 72 houirs.

Keep out of reach of children.
If swallowed, get medical help or contact a Poison Control Center right away.

Directions

■I Wet hands thoroughly
with product and allow to dry
without wiping■I for children|
under 6, use only under
adult supervision
■not recommended for
infants
Other information
1 1 Keep containers tightly
closed in a dry, cool and
well-ventilated place.
■Recommended storage
temperature: 32°F to 104°F
(0°C to 40°C)

Inactive ingredients

aloe barbadensis leaf juice,
fragrance, phenoxyethanol,
polysorbate 20, propylene
glycol, tocopheryl acetate,
water